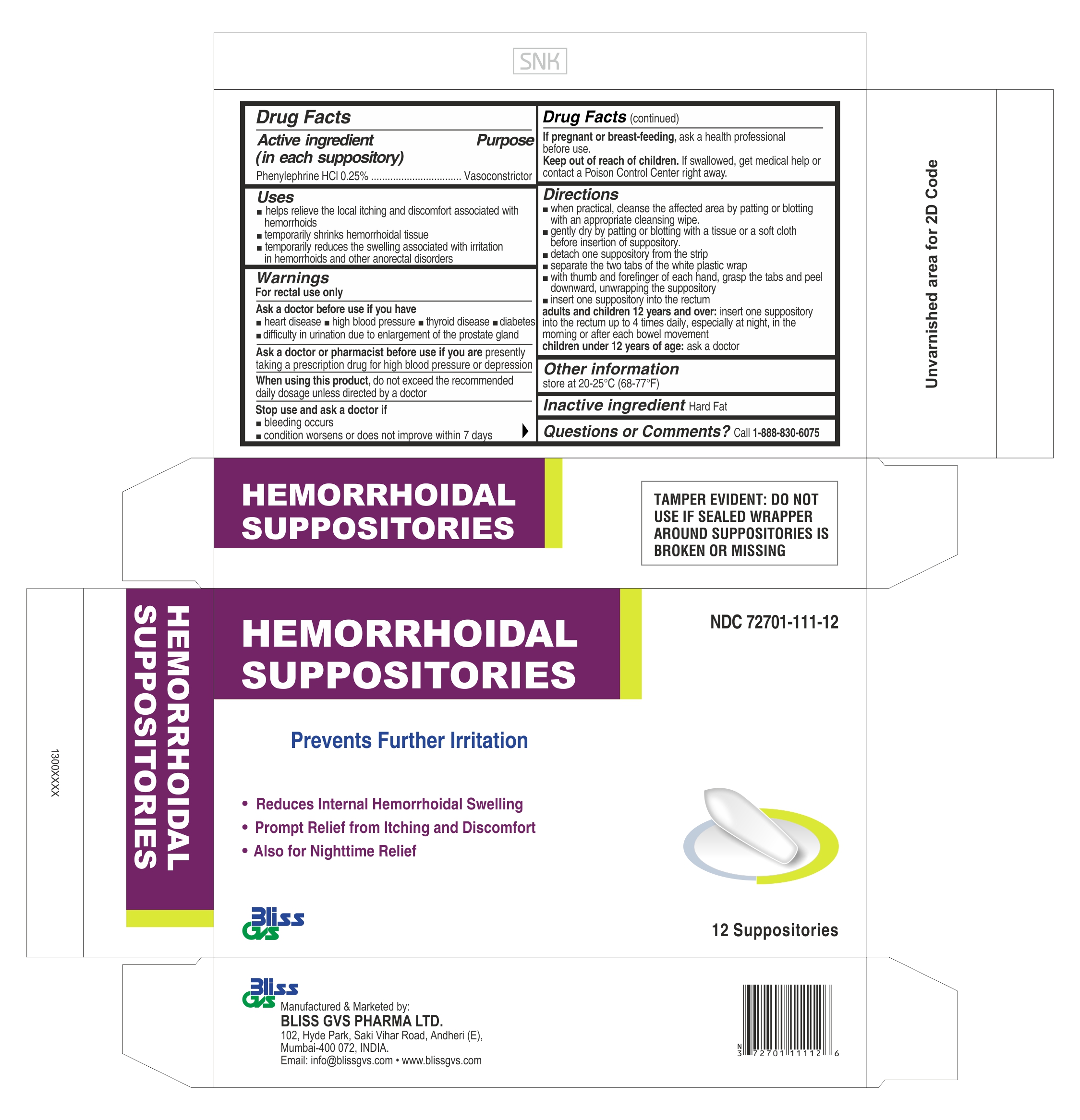 DRUG LABEL: BLISS GVS HEMORRHOIDAL
NDC: 72701-111 | Form: SUPPOSITORY
Manufacturer: Bliss GVS Pharma Limited
Category: otc | Type: HUMAN OTC DRUG LABEL
Date: 20241221

ACTIVE INGREDIENTS: PHENYLEPHRINE HYDROCHLORIDE 6.25 mg/1 1
INACTIVE INGREDIENTS: HARD FAT

BLISS GVS HEMORRHOIDAL – Phenylephrine Hcl Suppository

Active ingredient

(in each suppository)

Phenylephrine HCl 0.25%

Purpose

Vasoconstrictor

Uses

- helps relieve the local itching and discomfort associated with hemorrhoids
- temporarily shrinks hemorrhoidal tissue
- temporarily reduces the swelling associated with irritation in hemorrhoids and other anorectal disorders

Warnings

For rectal use only

Ask a doctor before use if you have

- heart disease
- high blood pressure
- thyroid disease
- diabetes
- difficulty in urination due to enlargement of the prostate gland

Ask a doctor or pharmacist before use if you are

presently taking a prescription drug for high blood pressure or depression

When using this product do not exceed the recommended daily dosage unless directed by a doctor

Stop use and ask a doctor if

- bleeding occurs
- condition worsens or does not improve within 7 days

PREGNANCY OR BREAST FEEDING

If pregnant or breast-feeding, ask a health professional before use

Keep out of reach of children. If swallowed, get medical help or contact a Poison Control Center right away.

Directions

- when practical, cleanse the affected area by patting or blotting with an appropriate cleansing wipe.
- gently dry by patting or blotting with a tissue or a soft cloth before insertion of suppository.
- detach one suppository from the strip
- separate the two tabs of the white plastic wrap
- with thumb and forefinger of each hand, grasp the tabs and peel downward, unwrapping the suppository
- insert one suppository into the rectum

adults and children 12 years and over: insert one suppository into the rectum up to 4 times daily, especially at night, in the morning or after each bowel movement

children under 12 years of age: ask a doctor

Other information

store at 20-25°C (68-77°F)

Inactive ingredient

Hard Fat

Questions or Comments?

Call 1-888-830-6075

TAMPER EVIDENT: DO NOT USE IF SEALED WRAPPER AROUND

SUPPOSITORIES IS BROKEN OR MISSING

PACKAGE LABEL

HEMORRHOIDAL SUPPOSITORIES

NDC 72701-111-12

Prevents Further Irritation

Reduces Internal Hemorrhoidal Swelling
Prompt Relief from Itching and Discomfort
Also for Nighttime Relief

Bliss GVS

12 Suppositories

Manufactured and Marketed by:

BLISS GVS PHARMA LTD.

102, Hyde Park, Saki Vihar Road, Andheri (E),

Mumbai-400 072, INDIA

Email: info@blissgvs.com • www.blissgvs.com